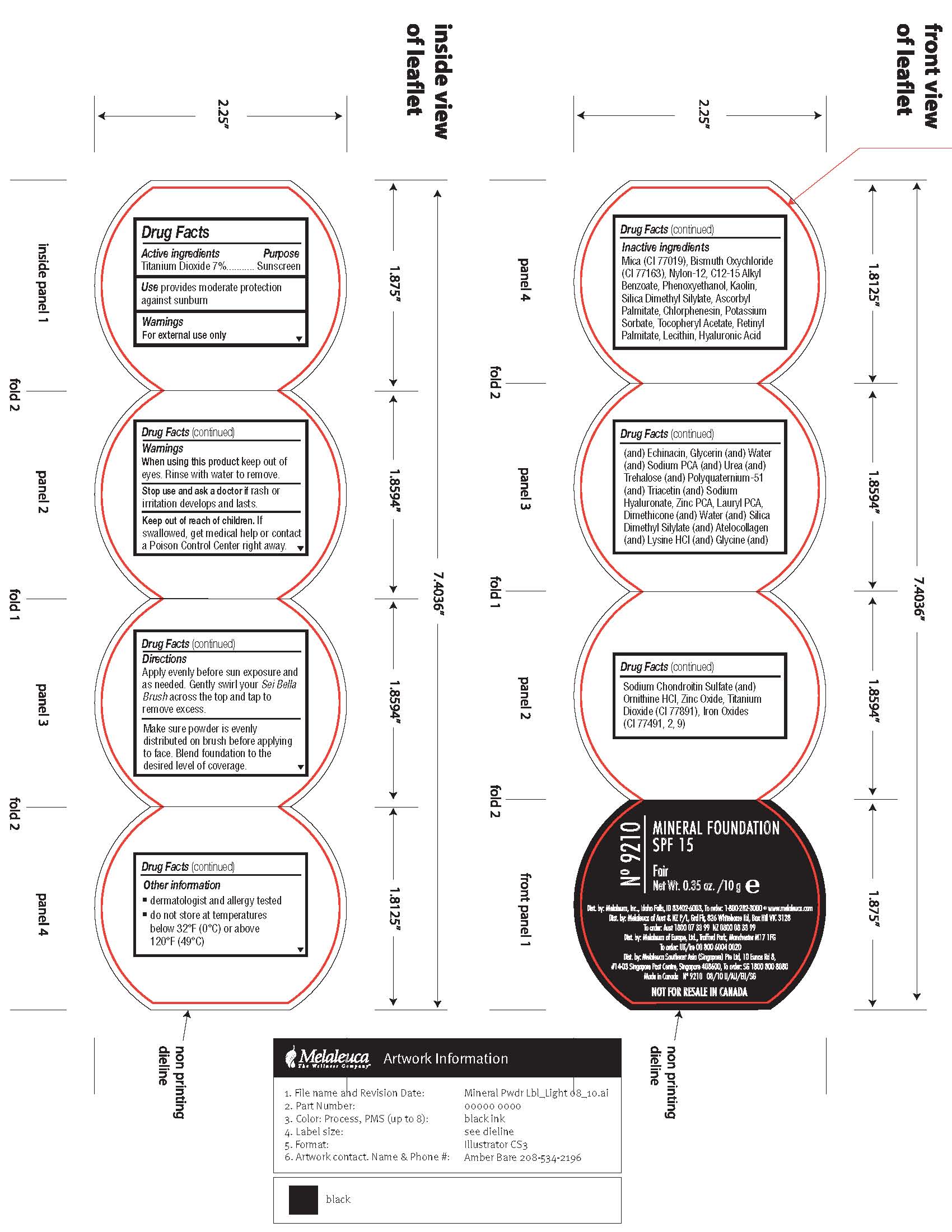 DRUG LABEL: SPF 15
NDC: 54473-174 | Form: POWDER
Manufacturer: Melaleuca, Inc.
Category: otc | Type: HUMAN OTC DRUG LABEL
Date: 20101214

ACTIVE INGREDIENTS: TITANIUM DIOXIDE 0.7 g/10 g
INACTIVE INGREDIENTS: MICA; BISMUTH OXYCHLORIDE; PHENOXYETHANOL; KAOLIN; ASCORBYL PALMITATE; CHLORPHENESIN; POTASSIUM SORBATE; VITAMIN A PALMITATE; LECITHIN, SOYBEAN; HYALURONIC ACID; GLYCERIN; WATER; UREA; TREHALOSE; TRIACETIN; DIMETHICONE; LYSINE HYDROCHLORIDE; GLYCINE; CHONDROITIN SULFATE (PORCINE); ZINC OXIDE; TITANIUM DIOXIDE; ALPHA-TOCOPHEROL ACETATE; C12-15 ALKYL BENZOATE; SODIUM PYRROLIDONE CARBOXYLATE; HYALURONATE SODIUM; ORNITHINE HYDROCHLORIDE; FERRIC OXIDE YELLOW; FERRIC OXIDE RED; FERROSOFERRIC OXIDE; ZINC PIDOLATE; SILICON DIOXIDE

Label of Mineral Foundation Fair

Directions

Apply evenly before sun exposure and as needed. Gently swirl your Sei Bella Brush across the tip and tap to remove excess.
Make sure powder is evenly distributed on brush before applying to face. Blend foundation to the desired level of coverage.

Other Information

- dermatologist and allergy tested

Other Information

- do not store at temperatures below 32°F (0°C) or above 120°F (49°C)

Inactive ingredients

Mica (CI 77019), Bismuth Oxichloride (CI 77163), Nylon-12, C12-15 Alkyl Benzoate, Phenoxyethanol, Kaolin, Silica Dimethyl Silylate, Ascorbyl Palmitate, Chlorphensin, Potassium Sorbate, Retinly Palmitate, Lecithin, Hyaluronic Acid (and) Echinacin, Glycerin (and) Water (and) Urea (and) Trehalose (and) Polyquaternium-51 (and) Triacetin (and) Sodium Hyaluronate, Zinc PCA, Lauryl PCA, Dimethicone (and) Water (and) Silica Dimethyl Silicylate (and) Atelocollagen (and) Lysine HCI (and) Glycine (and) Sodium Chrondrotin Sulfate (and) Ornithine HCI, Zinc Oxide, Titanium Oxide (CI 778914), Iron Oxides (CI 77491, 2, 9)

Active Ingredient Purpose

Titanium Dioxide 7%.......Sunscreen